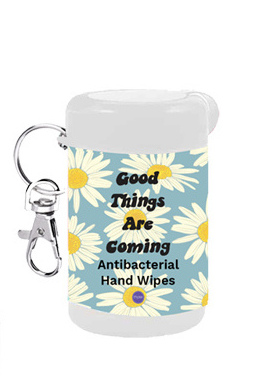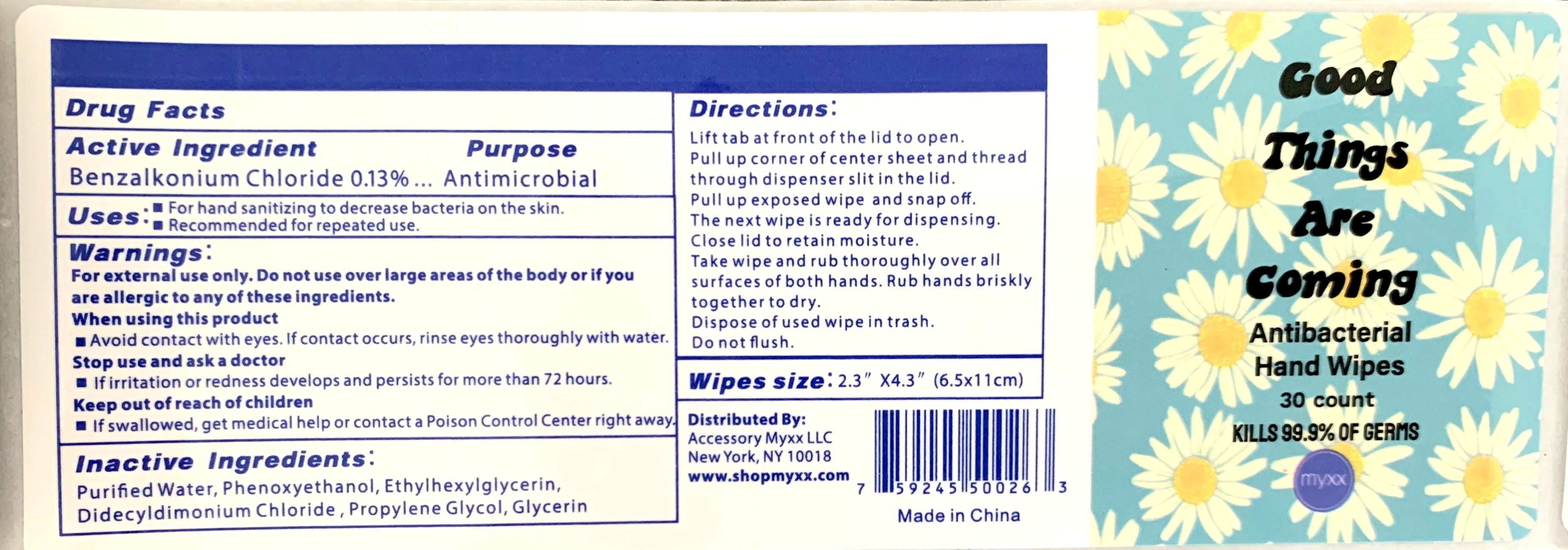 DRUG LABEL: hand wipes
NDC: 72619-0820 | Form: CLOTH
Manufacturer: Accessory Myxx LLC
Category: otc | Type: HUMAN OTC DRUG LABEL
Date: 20200828

ACTIVE INGREDIENTS: BENZALKONIUM CHLORIDE 0.13 g/100 mL
INACTIVE INGREDIENTS: WATER; PROPYLENE GLYCOL; ETHYLHEXYLGLYCERIN; PHENOXYETHANOL; GLYCERIN; DIDECYLDIMONIUM CHLORIDE

DOSAGE AND ADMINISTRATION

Recommended for repeated use.

WARNINGS

For external use only. Do not use over large areas of the body or if you are allergic to any of these ingredients.
When using this product avoid contact with eyes. If contact occurs, rinse eyes thoroughly with water.
Stop use and ask a doctor if irritation or redness develops and persists for more than 72 hours.
Keep out of reach of children.
If swallowed, get medical help or contact a Poison Control Center right away.

INACTIVE INGREDIENT

Water, Phenoxyethanol, Ethylhexylglycerin, Didecyldimonium Chloride , Propylene Glycol, Glycerin

INDICATIONS AND USAGE

Lift tab at front of the lid t o open.
Pull up corner of center sheet and thread
through di spenser slit i n the l id.
Pull up exposed wipe and snap off.
The next wipe i s ready for dispensing.
Close lid t o retain moisture.

Take wipe and rub thoroughly over all
surfaces of bot h hands. Rub hands briskly
together to dry.
Dispose of used wipe in trash.

Keep out of reach of children.

PURPOSE

For Hand Sanitizing to decrease bacteria on the skin. Recommended for repeated use.

ACTIVE INGREDIENT

Benzalkonium Chloride